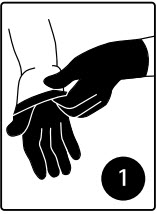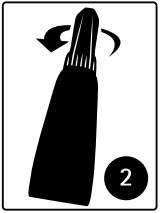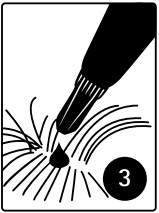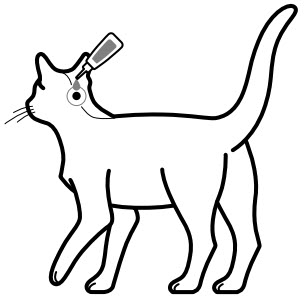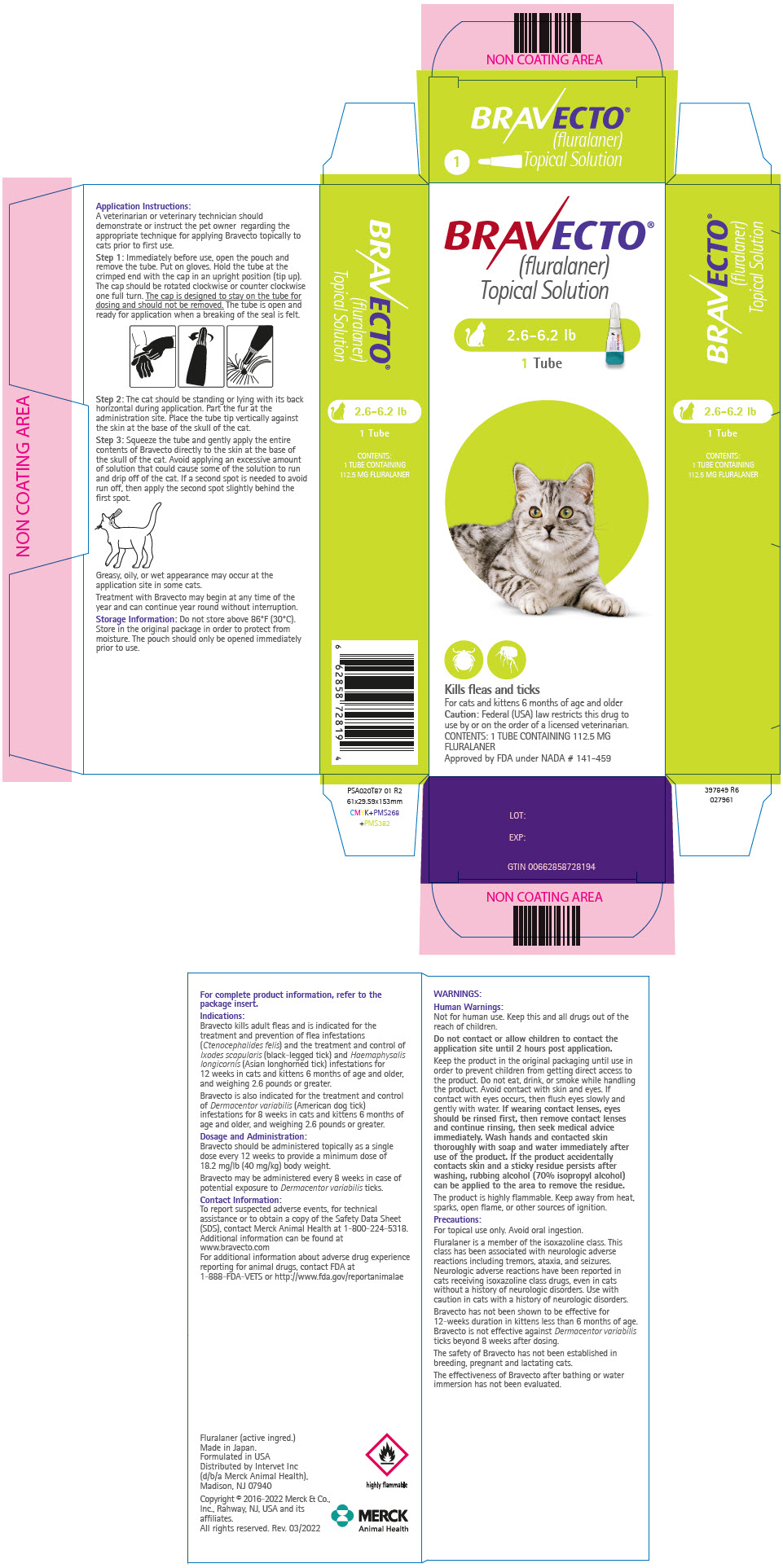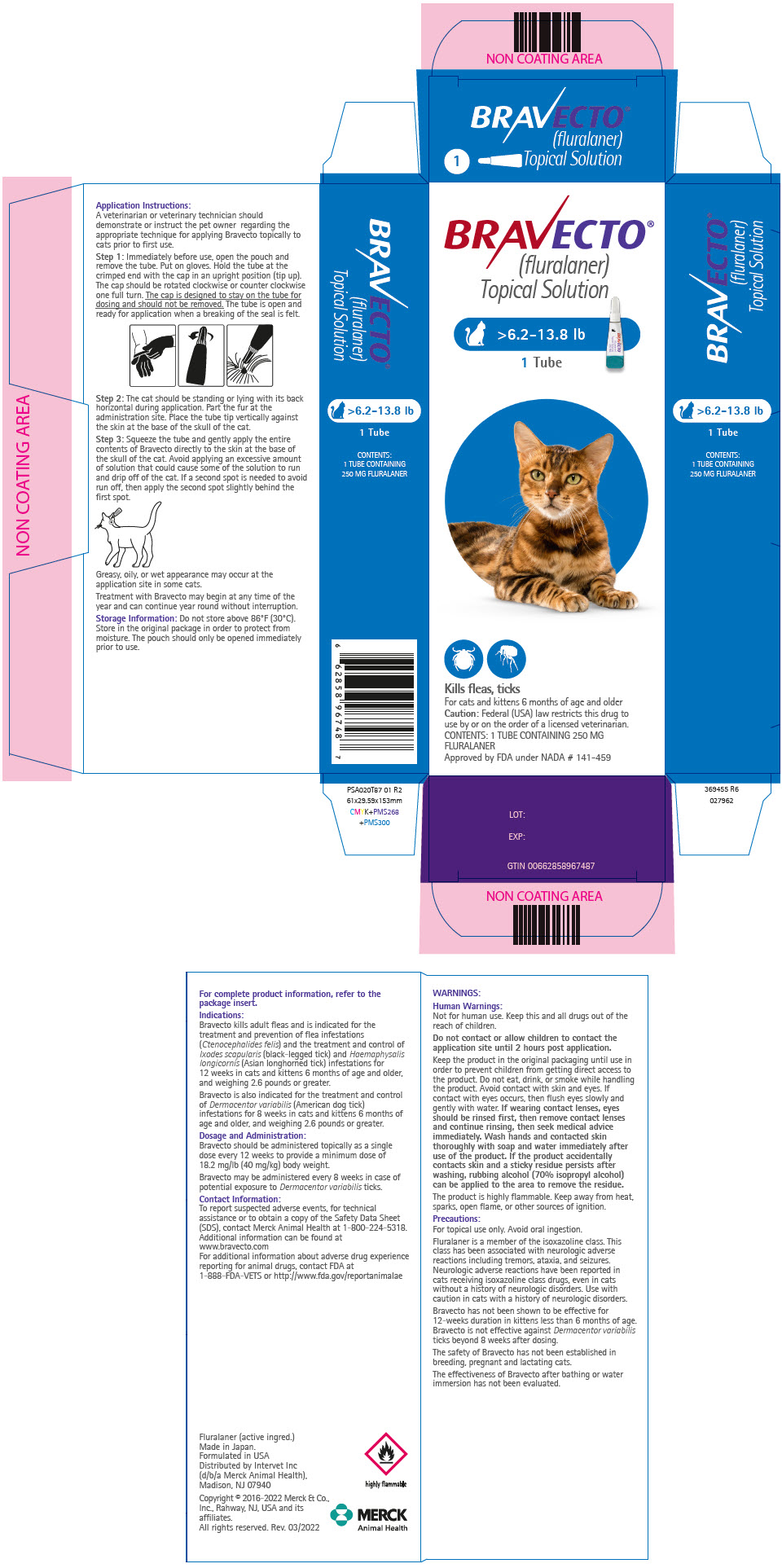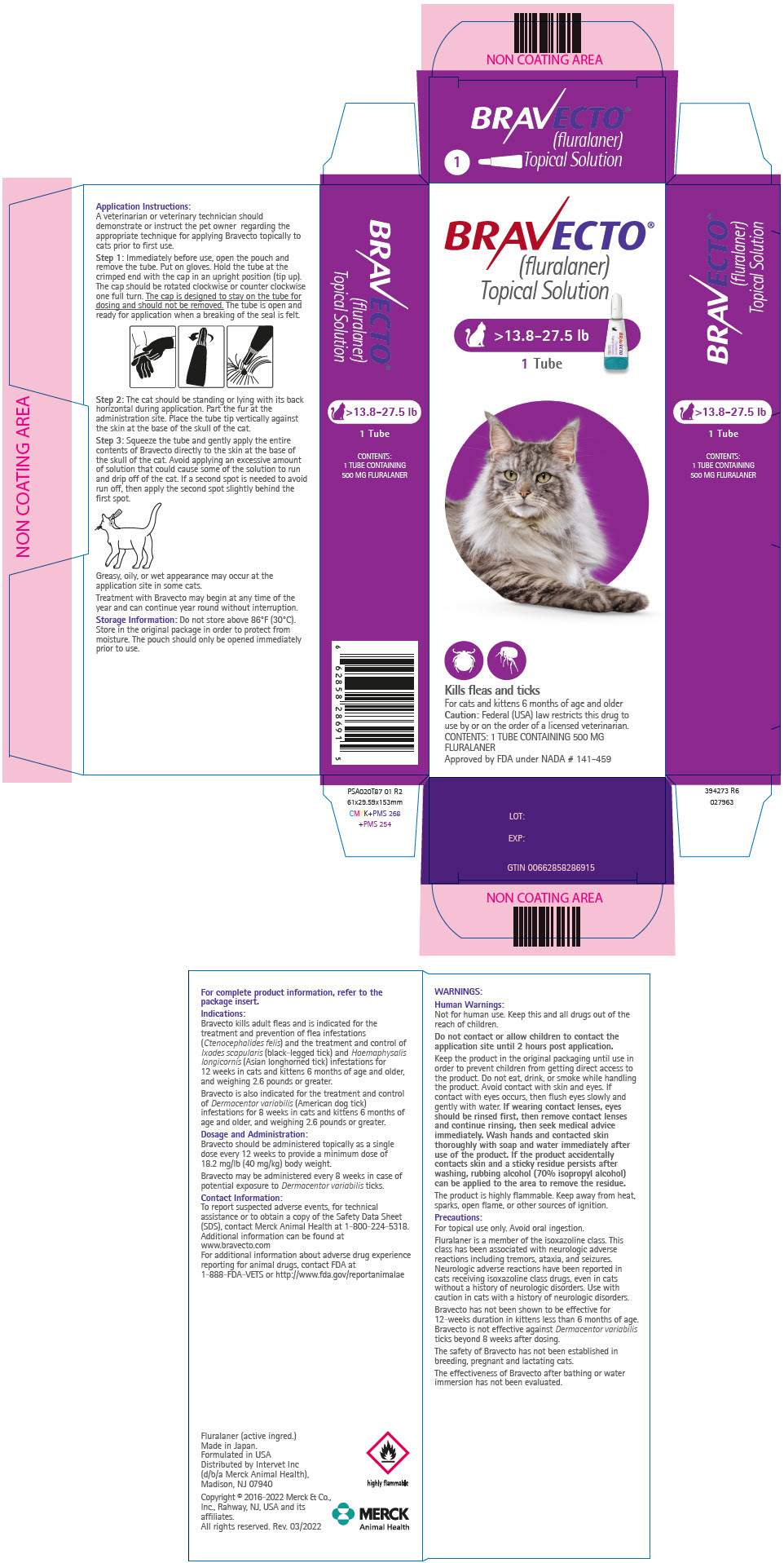 DRUG LABEL: Bravecto
NDC: 0061-5505 | Form: SOLUTION
Manufacturer: Merck Sharp & Dohme Corp.
Category: animal | Type: PRESCRIPTION ANIMAL DRUG LABEL
Date: 20241113

ACTIVE INGREDIENTS: FLURALANER 112.5 mg/1 1

BRAVECTO®
(fluralaner topical solution)
for Cats

Caution:

Federal (USA) law restricts this drug to use by or on the order of a licensed veterinarian.

Description:

Each tube is formulated to provide a minimum dose of 18.2 mg/lb (40 mg/kg) body weight. Each milliliter contains 280 mg of fluralaner.

The chemical name of fluralaner is (±)-4-[5-(3,5-dichlorophenyl)-5-(trifluoromethyl)-4,5-dihydroisoxazol-3-yl]-2-methyl-N-[2-oxo-2-(2,2,2 - trifluoroethylamino)ethyl]benzamide. Inactive ingredients: dimethylacetamide, glycofurol, diethyltoluamide, acetone

Indications:

Bravecto kills adult fleas and is indicated for the treatment and prevention of flea infestations (Ctenocephalides felis) and the treatment and control of Ixodes scapularis (black-legged tick) and Haemaphysalis longicornis (Asian longhorned tick) infestations for 12 weeks in cats and kittens 6 months of age and older, and weighing 2.6 pounds or greater.

Bravecto is also indicated for the treatment and control of Dermacentor variabilis (American dog tick) infestations for 8 weeks in cats and kittens 6 months of age and older, and weighing 2.6 pounds or greater.

Dosage and Administration:

Bravecto should be administered topically as a single dose every 12 weeks according to the Dosage Schedule below to provide a minimum dose of 18.2 mg/lb (40 mg/kg) body weight.

Bravecto may be administered every 8 weeks in case of potential exposure to Dermacentor variabilis ticks (see Effectiveness).

Dosage Schedule:

Body Weight Ranges (lb) | Fluralaner content (mg/tube) | Tubes Administered
2.6 – 6.2 | 112.5 | One
>6.2 – 13.8 | 250 | One
>13.8 – 27.5 [Cats over 27.5 lb should be administered the appropriate combination of tubes.] | 500 | One

A veterinarian or veterinary technician should demonstrate or instruct the pet owner regarding the appropriate technique for applying Bravecto topically to cats prior to first use.

Step 1: Immediately before use, open the pouch and remove the tube. Put on gloves. Hold the tube at the crimped end with the cap in an upright position (tip up). The cap should be rotated clockwise or counter clockwise one full turn. The cap is designed to stay on the tube for dosing and should not be removed. The tube is open and ready for application when a breaking of the seal is felt.

Step 2: The cat should be standing or lying with its back horizontal during application. Part the fur at the administration site. Place the tube tip vertically against the skin at the base of the skull of the cat.

Step 3: Squeeze the tube and gently apply the entire contents of Bravecto directly to the skin at the base of the skull of the cat. Avoid applying an excessive amount of solution that could cause some of the solution to run and drip off of the cat. If a second spot is needed to avoid run off, then apply the second spot slightly behind the first spot.

Greasy, oily, or wet appearance may occur at the application site in some cats.

Treatment with Bravecto may begin at any time of the year and can continue year round without interruption.

Contraindications:

There are no known contraindications for the use of the product.

WARNINGS

Human Warnings:

Not for human use. Keep this and all drugs out of the reach of children.

Do not contact or allow children to contact the application site until 2 hours post application.

Keep the product in the original packaging until use in order to prevent children from getting direct access to the product. Do not eat, drink, or smoke while handling the product. Avoid contact with skin and eyes. If contact with eyes occurs, then flush eyes slowly and gently with water. If wearing contact lenses, eyes should be rinsed first, then remove contact lenses and continue rinsing, then seek medical advice immediately. Wash hands and contacted skin thoroughly with soap and water immediately after use of the product. If the product accidentally contacts skin and a sticky residue persists after washing, rubbing alcohol (70% isopropyl alcohol) can be applied to the area to remove the residue.

The product is highly flammable. Keep away from heat, sparks, open flame or other sources of ignition.

Precautions:

For topical use only. Avoid oral ingestion. (see Animal Safety).

Fluralaner is a member of the isoxazoline class. This class has been associated with neurologic adverse reactions including tremors, ataxia, and seizures. Neurologic adverse reactions have been reported in cats receiving isoxazoline class drugs, even in cats without a history of neurologic disorders. Use with caution in cats with a history of neurologic disorders.

Bravecto has not been shown to be effective for 12-weeks duration in kittens less than 6 months of age. Bravecto is not effective against Dermacentor variabilis ticks beyond 8 weeks after dosing (see Effectiveness).

The safety of Bravecto has not been established in breeding, pregnant and lactating cats.

The effectiveness of Bravecto after bathing or water immersion has not been evaluated.

Adverse Reactions:

In a well-controlled U.S. field study, which included a total of 161 households and 311 treated cats (224 with fluralaner and 87 with a topical active control), there were no serious adverse reactions.

Percentage of Cats with Adverse Reactions (AR) in the Field Study
Adverse Reaction (AR) | Bravecto Group: Percent of Cats with the AR During the 105-Day Study (n=224 cats) | Active Control Group: Percent of Cats with the AR During the 84-Day Study (n=87 cats)
Vomiting | 7.6% | 6.9%
Pruritus | 5.4% | 11.5%
Diarrhea | 4.9% | 1.1%
Alopecia | 4.9% | 4.6%
Decreased Appetite | 3.6% | 0.0%
Lethargy | 3.1% | 2.3%
Scabs/Ulcerated Lesions | 2.2% | 3.4%

In the field study, two cats treated with fluralaner topical solution experienced ataxia. One cat became ataxic with a right head tilt 34 days after the first dose. The cat improved within one week of starting antibiotics. The ataxia and right head tilt, along with lateral recumbency, reoccurred 82 days after administration of the first dose. The cat recovered with antibiotics and was redosed with fluralaner topical solution 92 days after administration of the first dose, with no further abnormalities during the study. A second cat became ataxic 15 days after receiving its first dose and recovered the next day. The cat was redosed with fluralaner topical solution 82 days after administration of the first dose, with no further abnormalities during the study.

In a European field study, two cats from the same household experienced tremors, lethargy, and anorexia within one day of administration. The signs resolved in both cats within 48-72 hours.

In a European field study, there were three reports of facial dermatitis in humans after close contact with the application site which occurred within 4 days of application.

Post Approval Experience (2020):

The following adverse events are based on post-approval adverse drug experience reporting for fluralaner. Not all adverse events are reported to FDA/CVM. It is not always possible to reliably estimate the adverse event frequency or establish a causal relationship to product exposure using these data.

The following adverse events reported in cats are listed in decreasing order of reporting frequency:

Application site alopecia, lethargy, hypersalivation, anorexia, vomiting, behavioral disorders (including hyperactivity, hiding, and vocalization), generalized pruritus, application site disorders (including lesion, pruritus, and erythema), ataxia, alopecia, diarrhea, and muscle tremor.

Contact Information:

To report suspected adverse events, for technical assistance or to obtain a copy of the Safety Data Sheet (SDS), contact Merck Animal Health at 1-800-224-5318. Additional information can be found at www.bravecto.com

For additional information about adverse drug experience reporting for animal drugs, contact FDA at 1-888-FDA-VETS or http://www.fda.gov/reportanimalae

Clinical Pharmacology:

Peak fluralaner concentrations are achieved between 7 and 21 days following topical administration and the elimination half-life ranges between 11 and 13 days.

Mode of Action:

Fluralaner is for systemic use and belongs to the class of isoxazoline-substituted benzamide derivatives. Fluralaner is an inhibitor of the arthropod nervous system. The mode of action of fluralaner is the antagonism of the ligand-gated chloride channels (gamma-aminobutyric acid (GABA)-receptor and glutamate-receptor).

Effectiveness:

In a well-controlled European laboratory study, Bravecto killed 100% of fleas 8 hours after treatment and reduced the number of live fleas on cats by > 98% within 12 hours after treatment or post-infestation for 12 weeks. In well-controlled laboratory studies, Bravecto demonstrated > 94% effectiveness against Ixodes scapularis and Haemaphysalis longicornis 48 hours post-infestation for 12 weeks. Bravecto demonstrated > 98% effectiveness against Dermacentor variabilis 48 hours post-infestation for 8 weeks, but failed to demonstrate ≥ 90% effectiveness beyond 8 weeks.

In a well-controlled U.S. field study, a single dose of Bravecto reduced fleas by ≥99% for 12 weeks. Cats with signs of flea allergy dermatitis showed improvement in erythema, alopecia, papules, scales, crusts, and excoriation as a direct result of eliminating flea infestations.

Animal Safety:

Margin of Safety Study: In a margin of safety study, Bravecto was administered topically to 11- to 13-week (mean age 12 weeks)-old-kittens at 1, 3, and 5× the maximum labeled dose of 93 mg/kg at three, 8-week intervals (8 cats per group). The cats in the control group (0×) were treated with mineral oil.

There were no clinically-relevant, treatment-related effects on physical examination, body weights, food consumption, clinical pathology (hematology, clinical chemistries, coagulation tests, and urinalysis), gross pathology, histopathology, or organ weights. Cosmetic changes at the application site included matting/clumping/spiking of hair, wetness, or a greasy appearance.

Oral Safety Study: In a safety study, one dose of Bravecto topical solution was administered orally to 6- to 7-month-old-kittens at 1× the maximum labeled dose of 93 mg/kg. The kittens in the control group (0×) were administered saline orally.

There were no clinically-relevant, treatment-related effects on physical examination, body weights, food consumption, clinical pathology (hematology, clinical chemistries, coagulation tests, and urinalysis), gross pathology, histopathology, or organ weights. All treated kittens experienced salivation and four of six experienced coughing immediately after administration. One treated kitten experienced vomiting 2 hours after administration.

In a well-controlled field study Bravecto was used concurrently with other medications, such as vaccines, anthelmintics, antibiotics, steroids and sedatives. No adverse reactions were observed from the concurrent use of Bravecto with other medications.

Storage Conditions:

Do not store above 86°F (30°C). Store in the original package in order to protect from moisture. The pouch should only be opened immediately prior to use.

How Supplied:

Bravecto is available in three strengths for use in cats (112.5, 250, and 500 mg fluralaner per tube). Each tube is packaged individually in a pouch. Product may be supplied in 1 or 2 tubes per carton.

Approved by FDA under NADA # 141-459
Distributed by:

Intervet Inc (d/b/a Merck Animal Health), Madison, NJ 07940
Fluralaner (active ingred.) Made in Japan.
Formulated in USA

Copyright © 2016-2022 Merck & Co., Inc., Rahway, NJ, USA
and its affiliates. All rights reserved
Rev. 05/2022

380283 R5
027959

PRINCIPAL DISPLAY PANEL - 112.5 MG Tube Pouch Carton

BRAVECTO®
(fluralaner)
Topical Solution

2.6-6.2 lb
1 Tube

Kills fleas and ticks

For cats and kittens 6 months of age and older
Caution: Federal (USA) law restricts this drug to
use by or on the order of a licensed veterinarian.
CONTENTS: 1 TUBE CONTAINING 112.5 MG
FLURALANER
Approved by FDA under NADA # 141-459

PRINCIPAL DISPLAY PANEL - 250 MG Tube Pouch Carton

BRAVECTO®
(fluralaner)
Topical Solution

>6.2-13.8 lb
1 Tube

Kills fleas, ticks

For cats and kittens 6 months of age and older
Caution: Federal (USA) law restricts this drug to
use by or on the order of a licensed veterinarian.
CONTENTS: 1 TUBE CONTAINING 250 MG
FLURALANER
Approved by FDA under NADA # 141-459

PRINCIPAL DISPLAY PANEL - 500 MG Tube Pouch Carton

BRAVECTO®
(fluralaner)
Topical Solution

>13.8-27.5 lb
1 Tube

Kills fleas and ticks

For cats and kittens 6 months of age and older
Caution: Federal (USA) law restricts this drug to
use by or on the order of a licensed veterinarian.
CONTENTS: 1 TUBE CONTAINING 500 MG
FLURALANER
Approved by FDA under NADA # 141-459